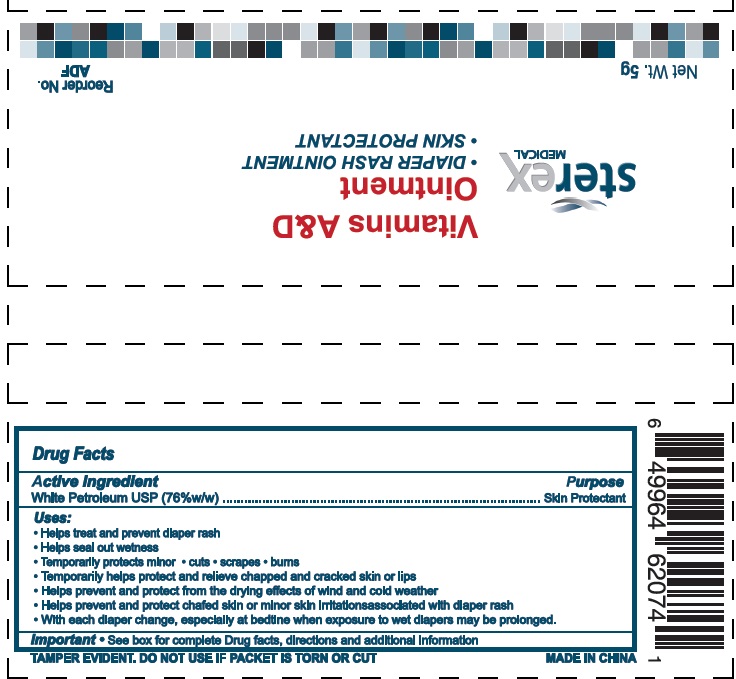 DRUG LABEL: Vitamins A and D
NDC: 72464-002 | Form: OINTMENT
Manufacturer: Tri-state Surgical Supply & Equipment Ltd.
Category: otc | Type: HUMAN OTC DRUG LABEL
Date: 20180722

ACTIVE INGREDIENTS: PETROLATUM 76 g/100 g
INACTIVE INGREDIENTS: MINERAL OIL; VITAMIN D; VITAMIN A

Active Ingredient:
White Petroleum USP (76%w/w)

Purpose:
Skin Protectant

Warnings:
For external use only

Stop use and ask a doctor if condition worsens, symptoms last more than 7 days or clear up and occur again in a few days.

KEEP OUT OF REACH OF CHILDREN

Keep out of the reach of children. If swallowed get medical help or contact a Poison Control Center right away.

DOSAGE AND ADMINISTRATION

Directions for Diaper Rash:

- Change wet and soiled diapers promptly.
- Cleanse the diaper area and allow to dry.
- Apply as needed.

Inactive Ingredients:

Mineral oil, Vitamin A, Vitamin D

Other Information:

- Store at room temperature 59-86 F(15-30C)
- Avoid excessive heat.

Uses:

- Helps treat and prevent diaper rash
- Helps seal out wetness
- Temporarily protects minor cuts, scrapes, burns
- Temporarily helps protect and relieve chapped and cracked skin or lips
- Helps prevent and protect from the drying effects of wind and cold weather
- Helps prevent and protect chafed skin or minor skin irritations associated with diaper rash
- With each diaper change, especially at bedtime when exposure to wet diapers may be prolonged

When using this product, do not get into eyes.

Do not use on

- deep puncture wounds
- animals bites
- serious burns